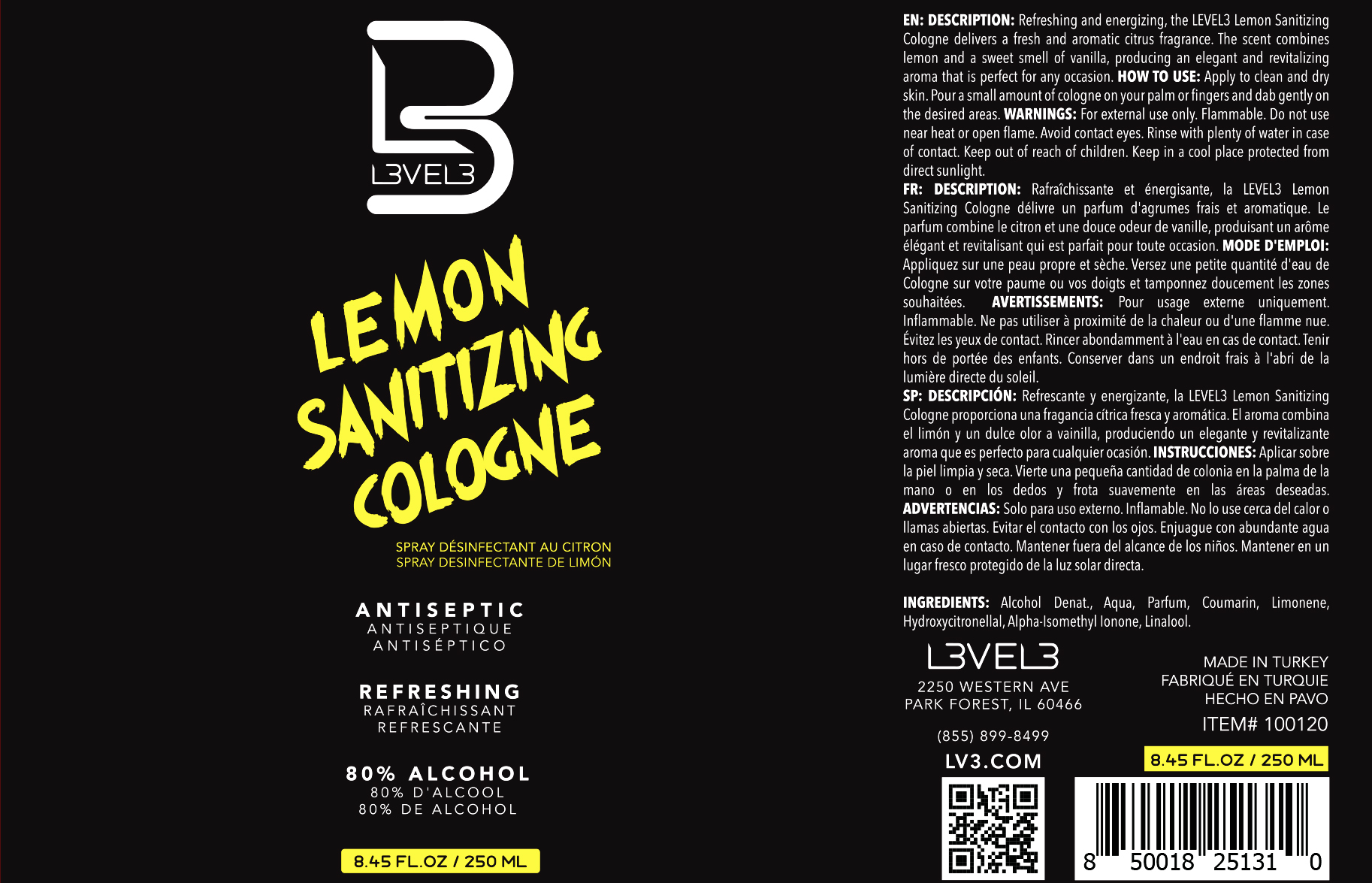 DRUG LABEL: Lemon Sanitizing Cologne
NDC: 80848-003 | Form: SPRAY
Manufacturer: L3VEL3 LLC
Category: otc | Type: HUMAN OTC DRUG LABEL
Date: 20201016

ACTIVE INGREDIENTS: ALCOHOL 80 mL/100 mL
INACTIVE INGREDIENTS: LINALOOL, (+/-)- 0.016 mL/100 mL; HYDROXYCITRONELLAL 0.032 mL/100 mL; ISOMETHYL-.ALPHA.-IONONE 0.025 mL/100 mL; COUMARIN 0.045 mL/100 mL; LIMONENE, (+/-)- 0.039 mL/100 mL; WATER

Lemon Sanitizing Cologne

Purpose

Sanitizing Cologne

Description

Refreshing and energizing, the LEVEL3 Lemon Cologne delivers a fresh and aromatic citrus fragrance. The scent combines lemon and a sweet smell of vanilla, producing an elegant and revitalizing aroma that is perfect for any occasion.

Directions:

Apply to clean and dry skin. Pour a small amount of cologne on your palm or fingers and dab gently on the desired areas.

Warnings

For external use only. Flammable. Do not use near heat or open flame. Avoid Contact with Eyes. In case of contact with eyes, rinse with plenty of water. Keep out of the reach of children. Keep in a cool place protected from direct sunlight.

Keep out of the reach of children.

Active Ingredient(s)

Alcohol

Inactive ingredients

Aqua, Parfum, Coumarin, Limonene, Hydroxycitronellal, Alpha-Isomethyl Ionone, Linalool

Package Label - Principal Display Panel

250 mL NDC: 80848-003-01